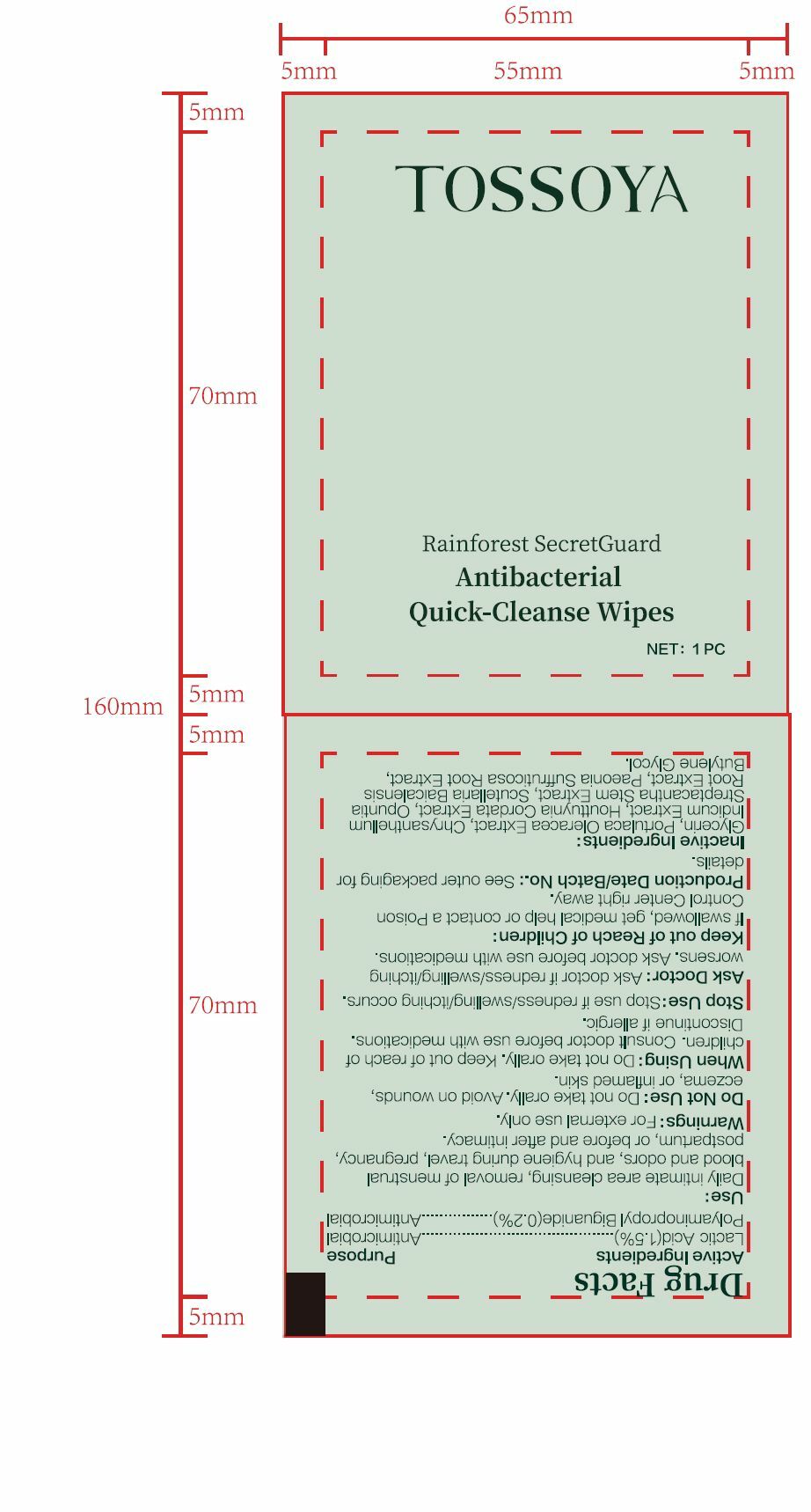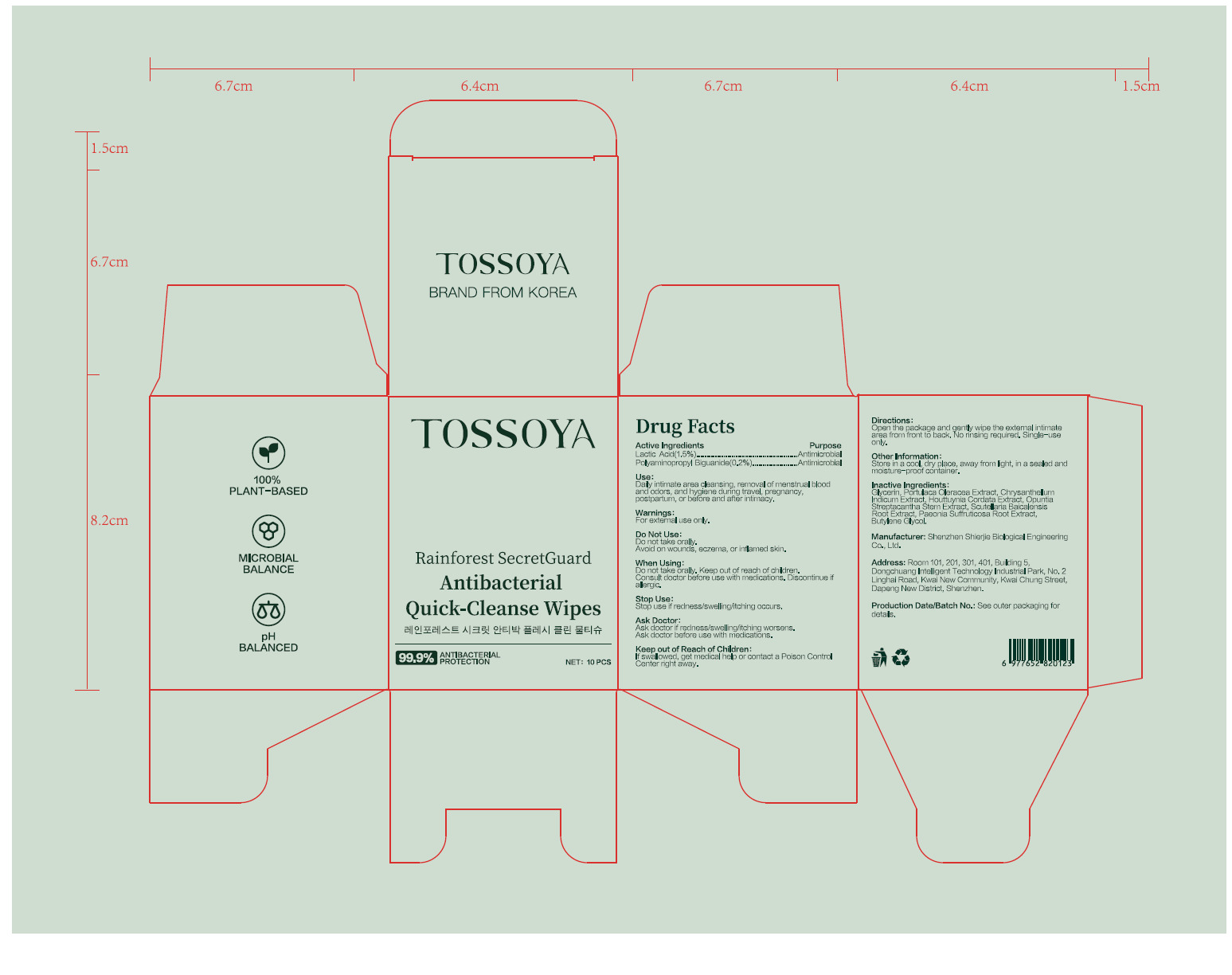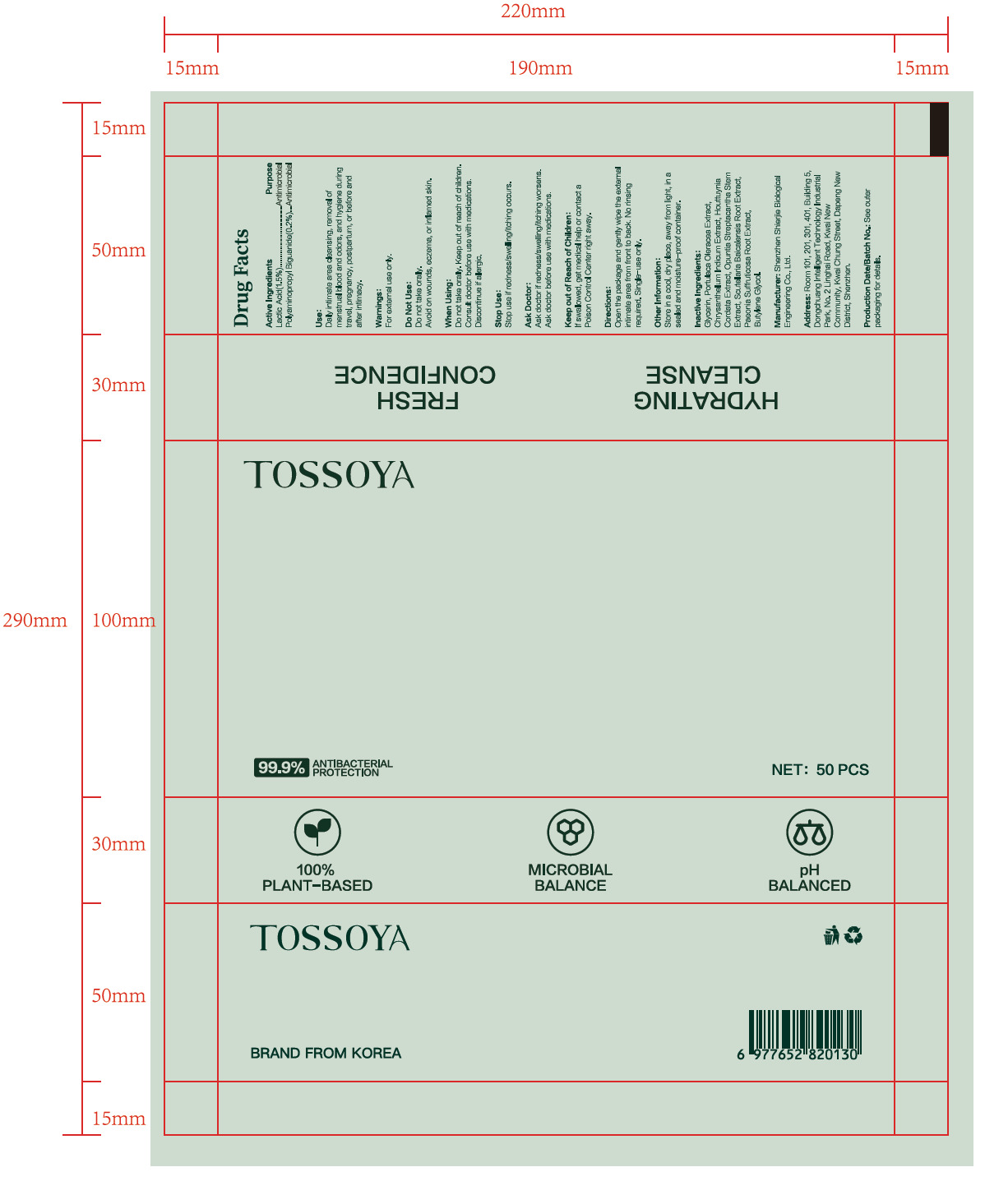 DRUG LABEL: TOSSOYA Rainforest SecretGuard Antibacterial Quick-Cleanse Wipes
NDC: 43116-045 | Form: CLOTH
Manufacturer: Shenzhen Shierjie Biological Engineering Co., LTD
Category: otc | Type: HUMAN OTC DRUG LABEL
Date: 20250901

ACTIVE INGREDIENTS: LACTIC ACID 1.5 U/100 U; POLYAMINOPROPYL BIGUANIDE 0.2 U/100 U
INACTIVE INGREDIENTS: PURSLANE; GLYCERIN; CHRYSANTHELLUM INDICUM TOP; HOUTTUYNIA CORDATA FLOWERING TOP; OPUNTIA STREPTACANTHA STEM; SCUTELLARIA BAICALENSIS ROOT; PAEONIA X SUFFRUTICOSA ROOT; BUTYLENE GLYCOL

43116-045

Active Ingredient

Lactic Acid 1.5%

Polyaminopropyl Biguanide 0.2%

Purpose

Antimicrobial

Use

Daily intimate area cleansing, removal of menstrual blood and odors, and hygiene during travel, pregnancy,
postpartum, or before and after intimacy.

Warnings

For external use only.

Do not use

Do not take orally.
Avoid on wounds, eczema, or inflamed skin.

When Using

Do not take orally. Keep out of reach of children.
Consult doctor before use with medications. Discontinue if allergic.

Stop Use

Stop use if redness/swelling/itching occurS.

Keep Oot Of Reach Of Children

If swallowed, get medical help or contact a Poison Control
Center right away.

Directions

Openthe package and genty wipe the exteral itimate
area from front to back. No rinsing required. Single-use
only.

Other information

Store in a cool, dry place, away from light, in a sealed and
moisture-proof container.

Inactive ingredients

Glycerin, Portulaca Oleracea Extract, Chrysanthellum Indicum Extract, Houttuynia Cordata Extract, Opuntia
Streptacantha Stem Extract, Scutellaria Baicalensis Root Extract, Paeonia Suffruticosa Root Bark Extract, Bifida
Ferment Filtrate, Butylene Glycol.